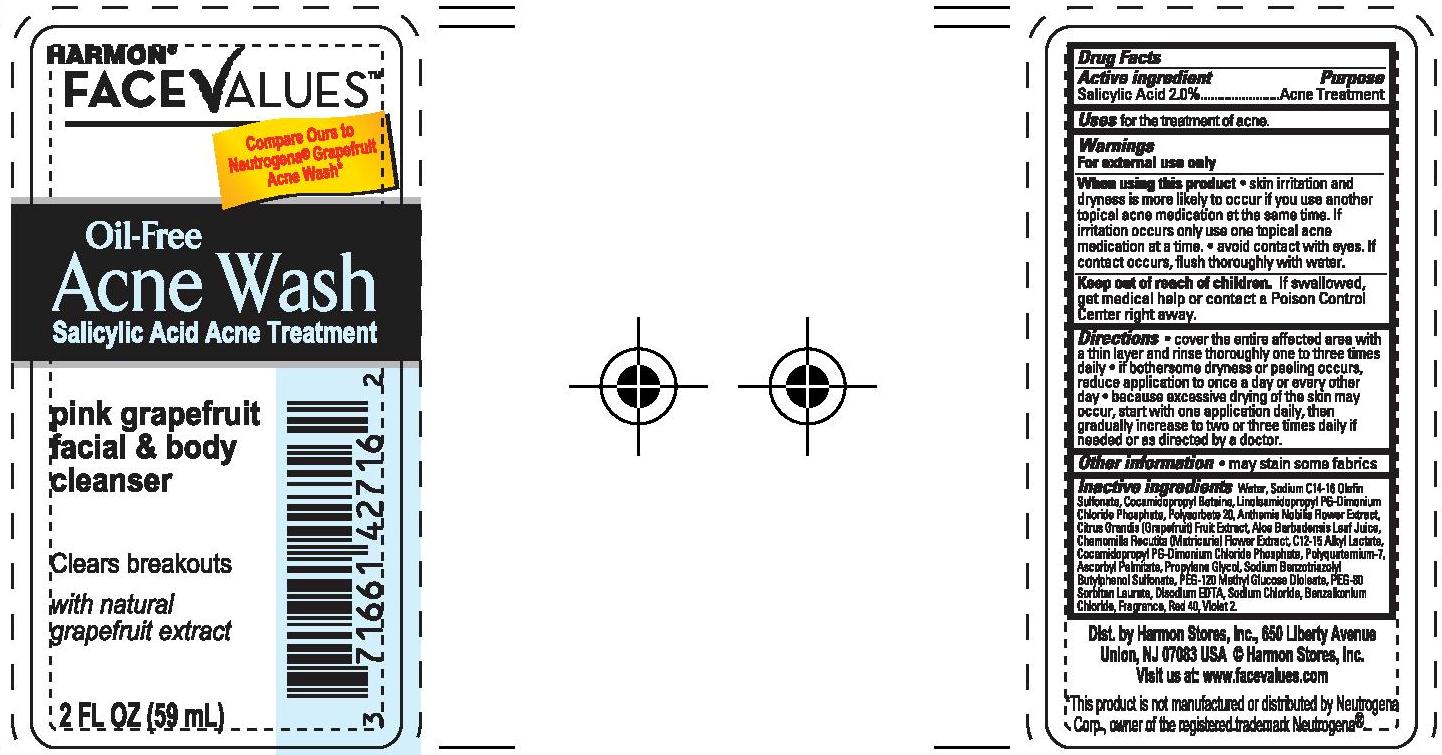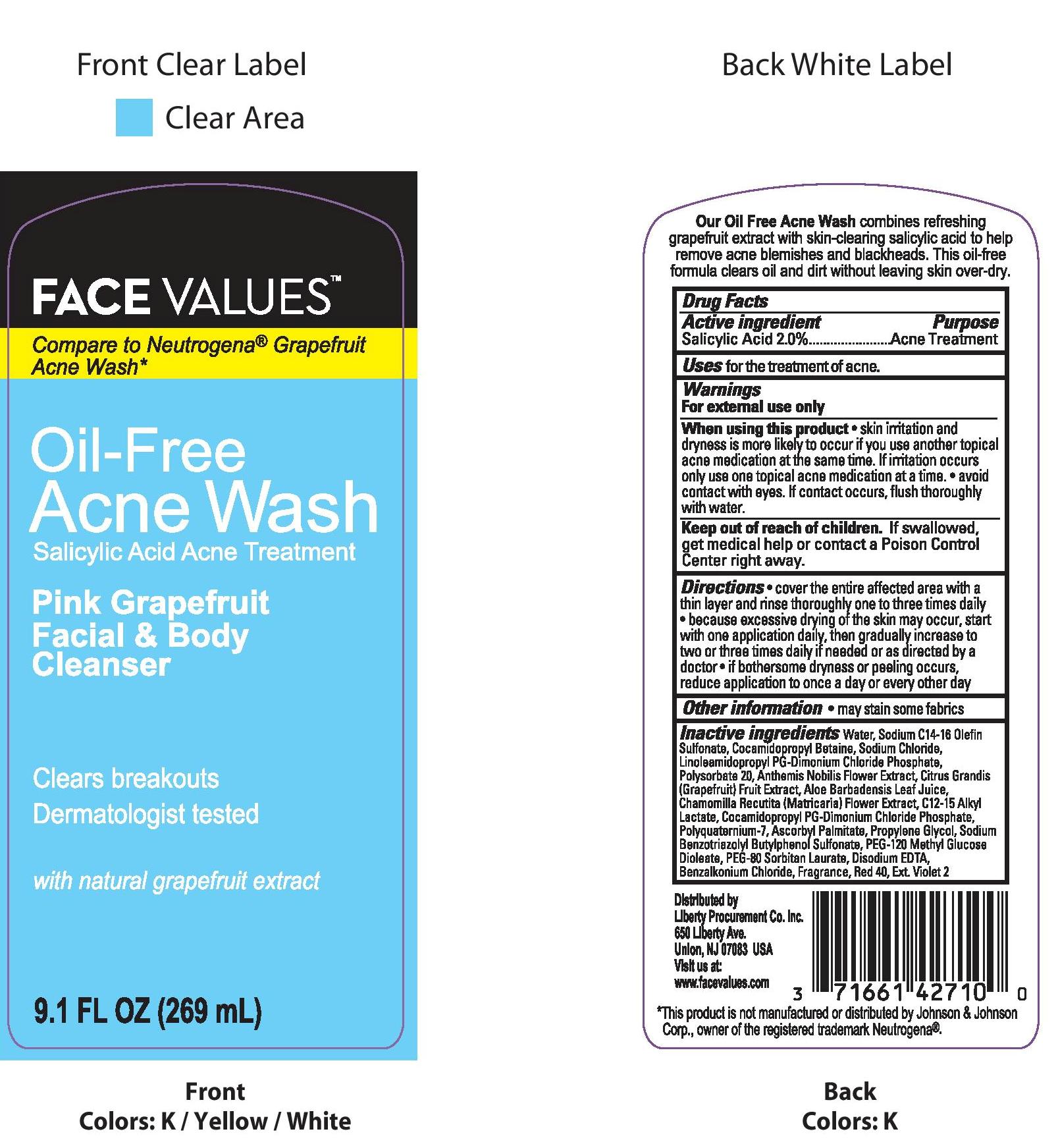 DRUG LABEL: ACNE WASH
NDC: 63940-053 | Form: LIQUID
Manufacturer: Harmon Stores Inc.
Category: otc | Type: HUMAN OTC DRUG LABEL
Date: 20241021

ACTIVE INGREDIENTS: SALICYLIC ACID 20 mg/1 mL
INACTIVE INGREDIENTS: WATER; SODIUM C14-16 OLEFIN SULFONATE; COCAMIDOPROPYL BETAINE; SODIUM CHLORIDE; LINOLEAMIDOPROPYL PG-DIMONIUM CHLORIDE PHOSPHATE; POLYSORBATE 20; CHAMAEMELUM NOBILE FLOWER; PUMMELO; ALOE VERA LEAF; CHAMOMILE; C12-15 ALKYL LACTATE; COCAMIDOPROPYL PG-DIMONIUM CHLORIDE PHOSPHATE; POLYQUATERNIUM-7 (70/30 ACRYLAMIDE/DADMAC; 1600 KD); ASCORBYL PALMITATE; PROPYLENE GLYCOL; SODIUM BENZOTRIAZOLYL BUTYLPHENOL SULFONATE; PEG-120 METHYL GLUCOSE DIOLEATE; PEG-80 SORBITAN LAURATE; EDETATE DISODIUM; BENZALKONIUM CHLORIDE; FD&C RED NO. 40; EXT. D&C VIOLET NO. 2

FACE VALUES OIL-FREE PINK GRAPEFRUIT FACIAL & BODY ACNE WASH

Active Ingredients

Salicylic Acid 2.0%

Purpose

Acne Treatment

Uses

for the treatment of acne.

Warnings

For external use only

When using this product • skin irritation and dryness is more likely to occur if you use another topical acne medication at the same time. If irritation occurs only use one topical acne medication at a time. • avoid contact with eyes. If contact occurs, flush thoroughly with water.

Keep out of reach of children. If swallowed, get medical help or contact a Poison Control Center immediately.

Directions

- cover the entire affected area with a thin layer and rinse thoroughly one to three times daily
- because excessive drying of the skin may occur, start with one application daily, then gradually increase to two or three times daily if needed or as directed by a doctor
- if bothersome dryness or peeling occurs, reduce application to once a day or every other day

Other information

- may stain some fabrics

Inactive Ingredients

water, sodium C14-16 olefin sulfonate, cocamidopropyl betaine, sodium chloride, linoleamidopropyl PG-dimonium chloride phosphate, polysorbate 20, anthemis nobilis flower extract, citrus grandis (grapefruit) fruit extract, aloe barbadensis leaf juice, chamomilla recutita (matricaria) flower extract, C12-15 alkyl lactate, cocamidopropyl PG-dimononium chloride phosphate, polyquaternium-7, ascorbyl palmitate, propylene glycol, sodium benzotriazolyl butylphenol sulfonate, PEG-120 methyl glucose dioleate, PEG-80 sorbitan laurate, disodium EDTA, benzalkonium chloride, fragrance, red 40, Ext. Violet 2

PACKAGE LABEL

FACE VALUES OIL-FREE PINK GRAPEFRUIT FACIAL & BODY ACNE WASH

9.1 FL OZ (269mL)

NDC 63940-053-54

FACE VALUES OIL-FREE PINK GRAPEFRUIT FACIAL & BODY ACNE WASH

2 FL OZ (59mL)

NDC 63940-053-61